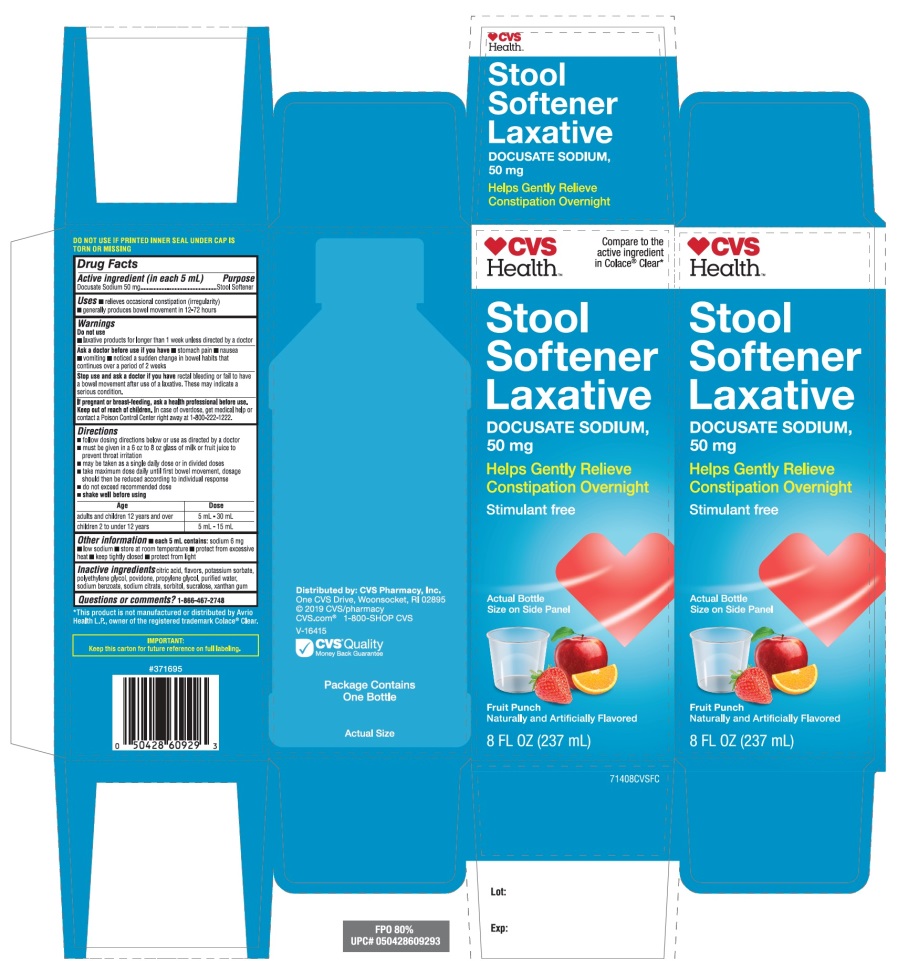 DRUG LABEL: CVS Stool Softener

NDC: 69842-714 | Form: LIQUID
Manufacturer: CVS PHARMACY, INC
Category: otc | Type: HUMAN OTC DRUG LABEL
Date: 20251209

ACTIVE INGREDIENTS: DOCUSATE SODIUM 50 mg/5 mL
INACTIVE INGREDIENTS: ANHYDROUS CITRIC ACID; POTASSIUM SORBATE; POLYETHYLENE GLYCOL, UNSPECIFIED; POVIDONE, UNSPECIFIED; PROPYLENE GLYCOL; WATER; SODIUM BENZOATE; SODIUM CITRATE, UNSPECIFIED FORM; SORBITOL; SUCRALOSE; XANTHAN GUM

CVS Health Stool Softener DOCUSATE LIQUID

Active ingredient (in each 5 mL teaspoonful)

Docusate Sodium 50 mg

Purpose

Stool Softener

Uses

- relieves occasional constipation (irregularity)
- generally produces bowel movement in 12-72 hours

Warnings

Do not use

- laxative products for longer than 1 week unless directed by a doctor

Ask a doctor before use if you have

- stomach pain
- nausea
- vomiting
- noticed a sudden change in bowel habits that continues over a period of 2 weeks

Stop use and ask a doctor ifrectal bleeding of fail to have a bowel movement after use of laxative. These may indicate a serious condition.

PREGNANCY OR BREAST FEEDING

If pregnant or breast feeding, ask a health professional before use.

Keep out of reach of children. In case of overdose, get medical help or contact a poison control Center right away at 1-800-222-1222.

Directions

- follow dosing directions below or take as directed by doctor
- must be given in a 6 to 8 oz glass of milk or fruit juice to prevent throat irritation
- may be taken as a single daily dose or in divided doses
- take maximum dose daily until first bowel movement, dosage should then be reduced according to individual response.
- do not exceed recommended dose
- shake well before using

Age | Dose
Adults and children 12 years and over | 5 mL-30 mL
Children 2 to under 12 years | 5 mL-15 mL

Other information

- each 5 mL contains:sodium 6 mg
- low sodium
- store at room temperature
- protect from excessive heat
- keep tightly closed
- protect from light

SAFETY SEALED: DO NOT USE IF PRINTED INNER SEAL UNDER CAP IS TORN OR MISSING

Inactive ingredients

citric acid, flavor, potassium sorbate, polyethylene glycol, povidone, propylene glycol, purified water, sodium benzoate, sodium citrate, sorbitol, sucralose, xanthan gum.

Principal Display Panel

NDC 69842-714-08

Compare to the active ingredient in Colace® Clear*

CVS Health™

Stool Softener Laxative
Docusate Sodium 50 mg

Helps Gently Relieves Constipation Overnight

Stimulant free

Fruit Punch

Naturally and Artificially Flavor
8 FL OZ (237 mL)

Package Contains One Bottle

Distributed by: CVS Pharmacy, Inc.

One CVS Drive, Woonsocket, RI 02895

© 2019 CVS/pharmacy

CVS.com®1-800-SHOP CVS

V-16415

CVS Quality Money Back Guarantee

*This product is not manufactured or distributed by Avrio Health L.P., owner of the registered trademark Colace®Clear.

IMPORTANT: Keep this carton for future reference on full labeling.